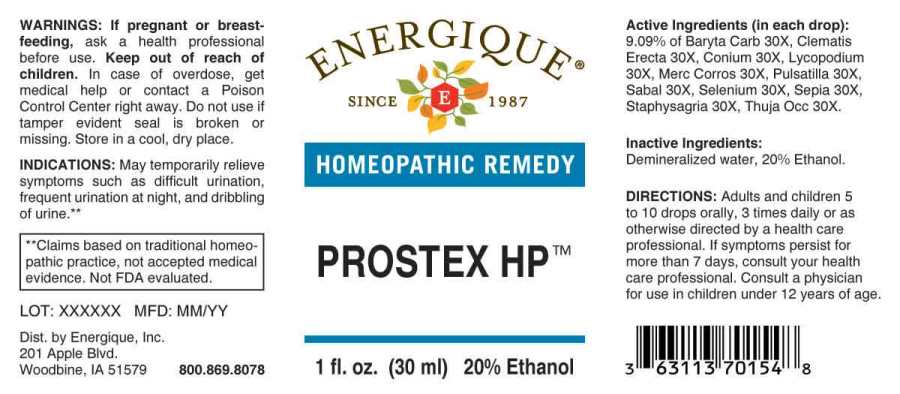 DRUG LABEL: Prostex
NDC: 44911-0288 | Form: LIQUID
Manufacturer: Energique, Inc.
Category: homeopathic | Type: HUMAN OTC DRUG LABEL
Date: 20230822

ACTIVE INGREDIENTS: BARIUM CARBONATE 30 [hp_X]/1 mL; CLEMATIS RECTA FLOWERING TOP 30 [hp_X]/1 mL; CONIUM MACULATUM FLOWERING TOP 30 [hp_X]/1 mL; LYCOPODIUM CLAVATUM SPORE 30 [hp_X]/1 mL; MERCURIC CHLORIDE 30 [hp_X]/1 mL; PULSATILLA PRATENSIS WHOLE 30 [hp_X]/1 mL; SAW PALMETTO 30 [hp_X]/1 mL; SELENIUM 30 [hp_X]/1 mL; SEPIA OFFICINALIS JUICE 30 [hp_X]/1 mL; DELPHINIUM STAPHISAGRIA SEED 30 [hp_X]/1 mL; THUJA OCCIDENTALIS LEAFY TWIG 30 [hp_X]/1 mL
INACTIVE INGREDIENTS: WATER; ALCOHOL

DRUG FACTS:

ACTIVE INGREDIENTS:

(in each drop): 9.09% of Baryta Carbonica 30X, Clematis Erecta 30X, Conium Maculatum 30X, Lycopodium Clavatum 30X, Mercurius Corrosivus 30X, Pulsatilla (Pratensis) 30X, Sabal Serrulata 30X, Selenium Metallicum 30X, Sepia 30X, Staphysagria 30X, Thuja Occidentalis 30X.

INDICATIONS:

May temporarily relieve symptoms such as difficult urination, frequent urination at night, and dribbling of urine.**
**Claims based on traditional homeopathic practice, not accepted medical evidence. Not FDA evaluated.

WARNINGS:

If pregnant or breast-feeding, ask a health professional before use.

Keep out of reach of children. In case of overdose, get medical help or contact a Poison Control Center right away.

Do not use if tamper evident seal is broken or missing. Store in a cool, dry place.

Keep out of reach of children. In case of overdose, get medical help or contact a Poison Control Center right away.

DIRECTIONS:

Adults and children 5 to 10 drops orally, 3 times daily or as otherwise directed by a health care professional. If symptoms persist for more than 7 days, consult your health care professional. Consult a physician for use in children under 12 years of age.

INDICATIONS:

May temporarily relieve symptoms such as difficult urination, frequent urination at night, and dribbling of urine.**
**Claims based on traditional homeopathic practice, not accepted medical evidence. Not FDA evaluated.

INACTIVE INGREDIENTS:

Demineralized water, 20% Ethanol

QUESTIONS:

Dist. by Energique, Inc.

201 Apple Blvd.

Woodbine, IA 51579 800.869.8078

PACKAGE LABEL DISPLAY:

ENERGIQUE
SINCE 1987
HOMEOPATHIC REMEDY
PROSTEX HP
1 fl. oz. (30 ml)